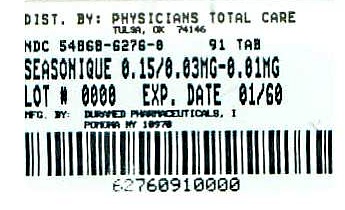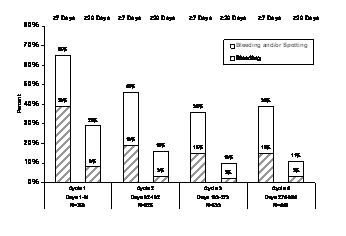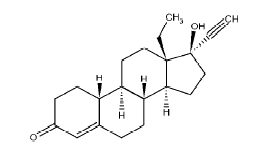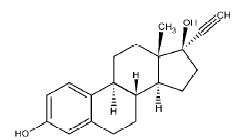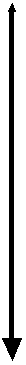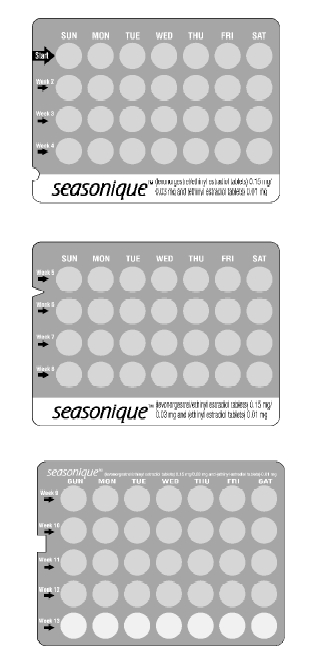 DRUG LABEL: Seasonique
NDC: 54868-6276 | Form: KIT | Route: ORAL
Manufacturer: Physicians Total Care, Inc.
Category: prescription | Type: HUMAN PRESCRIPTION DRUG LABEL
Date: 20100701

ACTIVE INGREDIENTS: LEVONORGESTREL 0.15 mg/1 1; ETHINYL ESTRADIOL 0.03 mg/1 1; ETHINYL ESTRADIOL 0.01 mg/1 1
INACTIVE INGREDIENTS: ANHYDROUS LACTOSE; D&C YELLOW NO. 10; FD&C BLUE NO. 1; FD&C YELLOW NO. 6; HYPROMELLOSES; LACTOSE MONOHYDRATE; MAGNESIUM STEARATE; CELLULOSE, MICROCRYSTALLINE; TITANIUM DIOXIDE; TRIACETIN; ANHYDROUS LACTOSE; D&C YELLOW NO. 10; FD&C YELLOW NO. 6; HYPROMELLOSES; MAGNESIUM STEARATE; CELLULOSE, MICROCRYSTALLINE; POLACRILIN POTASSIUM; POLYETHYLENE GLYCOL; TITANIUM DIOXIDE; POLYSORBATE 80

HIGHLIGHTS OF PRESCRIBING INFORMATION

These highlights do not include all the information needed to use Seasonique safely and effectively. See full prescribing information for Seasonique.
Seasonique (levonorgestrel/ethinyl estradiol tablets and ethinyl estradiol tablets) for oral use
Initial U.S. Approval: 1982

WARNING: CIGARETTE SMOKING AND SERIOUS CARDIOVASCULAR EVENTS

See full prescribing information for complete boxed warning.

- Women who are over 35 years old and smoke should not use Seasonique.
- Cigarette smoking increases the risk of serious cardiovascular events from combination oral contraceptive (COC) use.

1 INDICATIONS AND USAGE

Seasonique is an estrogen/progestin COC indicated for use by women to prevent pregnancy. (1)

2 DOSAGE AND ADMINISTRATION

Take one tablet daily by mouth at the same time every day for 91 days. (2)

3 DOSAGE FORMS AND STRENGTHS

Seasonique consists of 84 light blue-green tablets containing 0.15 mg levonorgestrel and 0.03 mg ethinyl estradiol, and 7 yellow tablets containing 0.01 mg ethinyl estradiol. (3)

4 CONTRAINDICATIONS

- A high risk of arterial or venous thrombotic diseases (4)
- Undiagnosed abnormal genital bleeding (4)
- Breast cancer or other estrogen- or progestin-sensitive cancer (4)
- Liver tumors or liver disease (4)
- Pregnancy (4)

5 WARNINGS AND PRECAUTIONS

- Vascular risks: Stop Seasonique if a thrombotic event occurs. Stop Seasonique at least 4 weeks before and through 2 weeks after major surgery. Start Seasonique no earlier than 4 weeks after delivery, in women who are not breastfeeding. (5.1)
- Liver disease: Discontinue Seasonique if jaundice occurs. (5.3)
- High blood pressure: Do not prescribe Seasonique for women with uncontrolled hypertension or hypertension with vascular disease. (5.4)
- Carbohydrate and lipid metabolic effects: Monitor prediabetic and diabetic women taking Seasonique. Consider an alternate contraceptive method for women with uncontrolled dyslipidemias. (5.6)
- Headache: Evaluate significant change in headaches and discontinue Seasonique if indicated. (5.7)
- Uterine bleeding: Evaluate irregular bleeding or amenorrhea. (5.8)

6 ADVERSE REACTIONS

The most common adverse reactions (≥5%) in clinical trials for Seasonique are irregular and/or heavy uterine bleeding, weight gain, and acne. (6)

To report SUSPECTED ADVERSE REACTIONS, contact Duramed Pharmaceuticals at 1-800-222-0190 or FDA 1-800-FDA-1088 or www.fda.gov/medwatch.

7 DRUG INTERACTIONS

Drugs or herbal products that induce certain enzymes, including CYP3A4, may decrease the effectiveness of COCs or increase breakthrough bleeding. Counsel patients to use a back-up method or alternative method of contraception when enzyme inducers are used with COCs. (7.1)

8 USE IN SPECIFIC POPULATIONS

- Nursing Mothers: Not recommended for nursing mothers; can decrease milk production. (8.3)

FULL PRESCRIBING INFORMATION

WARNING: CIGARETTE SMOKING AND SERIOUS CARDIOVASCULAR EVENTS

Cigarette smoking increases the risk of serious cardiovascular events from combination oral contraceptives (COC) use. This risk increases with age, particularly in women over 35 years of age, and with the number of cigarettes smoked. For this reason, COCs should not be used by women who are over 35 years of age and smoke. [See Contraindications (4).]

1 INDICATIONS AND USAGE

Seasonique® (levonorgestrel/ethinyl estradiol tablets and ethinyl estradiol tablets) is indicated for use by women to prevent pregnancy.

2 DOSAGE AND ADMINISTRATION

Take one tablet by mouth at the same time every day. The dosage of Seasonique is one light blue-green tablet containing levonorgestrel and ethinyl estradiol daily for 84 consecutive days, followed by one yellow ethinyl estradiol tablet for 7 days. To achieve maximum contraceptive effectiveness, Seasonique must be taken exactly as directed and at intervals not exceeding 24 hours.

Instruct the patient to begin taking Seasonique on the first Sunday after the onset of menstruation. If menstruation begins on a Sunday, the first light blue-green tablet is taken that day. One light blue-green tablet should be taken daily for 84 consecutive days, followed by one yellow tablet for 7 consecutive days. A non-hormonal back-up method of contraception (such as condoms or spermicide) should be used until a light blue-green tablet has been taken daily for 7 consecutive days. A scheduled period should occur during the 7 days that the yellow tablets are taken.

Begin the next and all subsequent 91-day cycles without interruption on the same day of the week (Sunday) on which the patient began her first dose of Seasonique, following the same schedule: 84 days taking a light blue-green tablet followed by 7 days taking a yellow tablet. If the patient does not immediately start her next pill pack, she should protect herself from pregnancy by using a non-hormonal back-up method of contraception until she has taken a light blue-green tablet daily for 7 consecutive days.

If unscheduled spotting or bleeding occurs, instruct the patient to continue on the same regimen. If the bleeding is persistent or prolonged, advise the patient to consult her healthcare provider.

For patient instructions regarding missed pills, see FDA-Approved Patient Labeling.

For postpartum women who are not breastfeeding, start Seasonique no earlier than four to six weeks postpartum due to increased risk of thromboembolism. If the patient starts on Seasonique postpartum and has not yet had a period, evaluate for possible pregnancy, and instruct her to use an additional method of contraception until she has taken a light blue-green tablet for 7 consecutive days.

3 DOSAGE FORMS AND STRENGTHS

Seasonique tablets (levonorgestrel/ethinyl estradiol tablets and ethinyl estradiol tablets) are available in Extended-Cycle Tablet Dispensers, each containing a 13-week supply of tablets: 84 light blue-green tablets, each containing 0.15 mg of levonorgestrel and 0.03 mg ethinyl estradiol, and 7 yellow tablets each containing 0.01 mg of ethinyl estradiol. The light blue-green tablets are round, film-coated, biconvex, unscored tablets debossed with stylized b on one side and 555 on the other side. The yellow tablets are round, biconvex, film-coated, unscored tablets debossed with stylized b on one side and 556 on the other side.

4 CONTRAINDICATIONS

Do not prescribe Seasonique to women who are known to have the following:

- A high risk of arterial or venous thrombotic diseases. Examples include women who are known to:
  - Smoke, if over age 35 [see Boxed Warning and Warnings and Precautions (5.1)].
  - Have deep vein thrombosis or pulmonary embolism, now or in the past [see Warnings and Precautions (5.1)]
  - Have cerebrovascular disease [see Warnings and Precautions (5.1)]
  - Have coronary artery disease [see Warnings and Precautions (5.1)]
  - Have thrombogenic valvular or thrombogenic rhythm diseases of the heart (for example, subacute bacterial endocarditis with valvular disease, or atrial fibrillation) [see Warnings and Precautions (5.1)]
  - Have inherited or acquired hypercoagulopathies [see Warnings and Precautions (5.1)]
  - Have uncontrolled hypertension [see Warnings and Precautions (5.4)].
  - Have diabetes with vascular disease [see Warnings and Precautions (5.6)].
  - Have headaches with focal neurological symptoms or have migraine headaches with or without aura if over age 35 [see Warnings and Precautions (5.7)].
- Undiagnosed abnormal genital bleeding [see Warnings and Precautions (5.8)].
- Breast cancer or other estrogen- or progestin-sensitive cancer, now or in the past [see Warnings and Precautions (5.2)].
- Liver tumors, benign or malignant, or liver disease [see Warnings and Precautions (5.3) and Use in Specific Populations (8.6)].
- Pregnancy, because there is no reason to use COCs during pregnancy [see Warnings and Precautions (5.9) and Use in Specific Populations (8.1)].

5 WARNINGS AND PRECAUTIONS

5.1 Thrombotic and Other Vascular Events

Stop Seasonique if an arterial or deep venous thrombotic event occurs. Although the use of COCs increases the risk of venous thromboembolism, pregnancy increases the risk of venous thromboembolism as much or more than the use of COCs. The risk of venous thromboembolism in women using COCs is 3 to 9 per 10,000 woman-years. The excess risk is highest during the first year of use of a COC. Use of COCs also increases the risk of arterial thromboses such as strokes and myocardial infarctions, especially in women with other risk factors for these events. The risk of thromboembolic disease due to COCs gradually disappears after COC use is discontinued.

Use of Seasonique provides women with more hormonal exposure on a yearly basis than conventional monthly oral contraceptives containing the same strength synthetic estrogens and progestins (an additional 9 and 13 weeks of exposure to progestin and estrogen, respectively, per year).

If feasible, stop Seasonique at least 4 weeks before and through 2 weeks after major surgery or other surgeries known to have an elevated risk of thromboembolism.

Start Seasonique no earlier than 4-6 weeks after delivery, in women who are not breastfeeding. The risk of postpartum thromboembolism decreases after the third postpartum week, whereas the risk of ovulation increases after the third postpartum week.

COCs have been shown to increase both the relative and attributable risks of cerebrovascular events (thrombotic and hemorrhagic strokes), although, in general, the risk is greatest among older (>35 years of age), and hypertensive women who also smoke. COCs also increase the risk for stroke in women with other underlying risk factors.

Oral contraceptives must be used with caution in women with cardiovascular disease risk factors.

Stop Seasonique if there is unexplained loss of vision, proptosis, diplopia, papilledema, or retinal vascular lesions. Evaluate for retinal vein thrombosis immediately.

5.2 Carcinoma of the Breast and Cervix

Women who currently have or have had breast cancer should not use Seasonique because breast cancer may be hormonally sensitive.

There is substantial evidence that COCs do not increase the incidence of breast cancer. Although some past studies have suggested that COCs might increase the incidence of breast cancer, more recent studies have not confirmed such findings.

Some studies suggest that COCs are associated with an increase in the risk of cervical cancer or intraepithelial neoplasia. However, there is controversy about the extent to which these findings are due to differences in sexual behavior and other factors.

5.3 Liver Disease

Discontinue Seasonique if jaundice develops. Steroid hormones may be poorly metabolized in patients with impaired liver function. Acute or chronic disturbances of liver function may necessitate the discontinuation of COC use until markers of liver function return to normal and COC causation has been excluded.

Hepatic adenomas are associated with COC use. An estimate of the attributable risk is 3.3 cases/100,000 COC users. Rupture of hepatic adenomas may cause death through intra-abdominal hemorrhage.

Studies have shown an increased risk of developing hepatocellular carcinoma in long-term (> 8 years) COC users. However, the attributable risk of liver cancers in COC users is less than one case per million users.

Oral contraceptive-related cholestasis may occur in women with a history of pregnancy-related cholestasis. Women with a history of COC-related cholestasis may have the condition recur with subsequent COC use.

5.4 High Blood Pressure

For women with well-controlled hypertension, monitor blood pressure and stop Seasonique if blood pressure rises significantly. Women with uncontrolled hypertension or hypertension with vascular disease should not use COCs.

An increase in blood pressure has been reported in women taking COCs, and this increase is more likely in older women and with extended duration of use. The incidence of hypertension increases with increasing concentration of progestin.

5.5 Gallbladder Disease

Studies suggest a small increased relative risk of developing gallbladder disease among COC users.

5.6 Carbohydrate and Lipid Metabolic Effects

Carefully monitor prediabetic and diabetic women who are taking Seasonique. COCs may decrease glucose tolerance in a dose-related fashion.

Consider alternative contraception for women with uncontrolled dyslipidemias. A small proportion of women will have adverse lipid changes while on COCs.

Women with hypertriglyceridemia, or a family history thereof, may be at an increased risk of pancreatitis when using COCs.

5.7 Headache

If a woman taking Seasonique develops new headaches that are recurrent, persistent, or severe, evaluate the cause and discontinue Seasonique if indicated.

An increase in frequency or severity of migraine during COC use (which may be prodromal of a cerebrovascular event) may be a reason for immediate discontinuation of the COC.

5.8 Bleeding Irregularities

Unscheduled (breakthrough) bleeding and spotting sometimes occur in patients on COCs, especially during the first 3 months of use. If bleeding persists, check for causes such as pregnancy or malignancy. If pathology and pregnancy are excluded, bleeding irregularities may resolve over time or with a change to a different COC.

When prescribing Seasonique, the convenience of fewer planned menses (4 per year instead of 13 per year) should be weighed against the inconvenience of increased unscheduled bleeding and/or spotting. The primary clinical trial (PSE-301) that evaluated the efficacy of Seasonique also assessed unscheduled bleeding. The participants in the 12-month clinical trial (N=1,006) completed the equivalent of 8,681 28-day cycles of exposure and were composed primarily of women who had used oral contraceptives previously (89%) as opposed to new users (11%). A total of 82 (8.2%) of the women discontinued Seasonique, at least in part, due to bleeding or spotting.

Scheduled (withdrawal) bleeding and/or spotting remained fairly constant over time, with an average of 3 days of bleeding and/or spotting per each 91-day cycle. Unscheduled bleeding and unscheduled spotting decreased over successive 91-day cycles. Table 1 below presents the number of days with unscheduled bleeding in treatment cycles 1 and 4. Table 2 presents the number of days with unscheduled spotting in treatment cycles 1 and 4.

Table 1: Total Number of Days with Unscheduled Bleeding
91-Day Treatment Cycle | Days per 84-Day Interval |  |  |  | Days per 28-Day Interval
91-Day Treatment Cycle | Q1 | Median | Q3 | Mean | Mean
1st | 1 | 4 | 10 | 6.9 | 1.7
4th | 0 | 1 | 4 | 3.2 | 0.8
Q1=Quartile 1: 25% of women had ≤ this number of days of unscheduled bleeding
Median: 50% of women had ≤ this number of days of unscheduled bleeding
Q3=Quartile 3: 75% of women had ≤ this number of days of unscheduled bleeding

Table 2: Total Number of Days with Unscheduled Spotting
91-Day Treatment Cycle | Days per 84-Day Interval |  |  |  | Days per 28-Day Interval
91-Day Treatment Cycle | Q1 | Median | Q3 | Mean | Mean
1st | 1 | 4 | 11 | 7.4 | 1.9
4th | 0 | 2 | 7 | 4.4 | 1.1
Q1=Quartile 1: 25% of women had ≤ this number of days of unscheduled spotting
Median: 50% of women had ≤ this number of days of unscheduled spotting
Q3=Quartile 3: 75% of women had ≤ this number of days of unscheduled spotting.

Figure 1 shows the percentage of Seasonique subjects participating in trial PSE-301 with ≥ 7 days or ≥ 20 days of unscheduled bleeding and/or spotting, or only unscheduled bleeding, during each 91-day treatment cycle.

Figure 1. Percent of Women Taking Seasonique who Reported Unscheduled Bleeding and/or Spotting or only Unscheduled Bleeding

Amenorrhea sometimes occurs in women who are using COCs. Pregnancy should be ruled out in the event of amenorrhea. Some women may encounter amenorrhea or oligomenorrhea after stopping COCs, especially when such a condition was pre-existent.

5.9 COC Use Before or During Early Pregnancy

Extensive epidemiological studies have revealed no increased risk of birth defects in women who have used oral contraceptives prior to pregnancy. Studies also do not suggest a teratogenic effect, particularly in so far as cardiac anomalies and limb-reduction defects are concerned, when taken inadvertently during early pregnancy. Oral contraceptive use should be discontinued if pregnancy is confirmed.

The administration of oral contraceptives to induce withdrawal bleeding should not be used as a test for pregnancy [see Use in Specific Populations (8.1)].

5.10 Emotional Disorders

Women with a history of depression should be carefully observed and Seasonique discontinued if depression recurs to a serious degree.

5.11 Interference with Laboratory Tests

The use of COCs may change the results of some laboratory tests, such as coagulation factors, lipids, glucose tolerance, and binding proteins. Women on thyroid hormone replacement therapy may need increased doses of thyroid hormone because serum concentrations of thyroid binding globulin increase with use of COCs.

5.12 Monitoring

A woman who is taking COCs should have a yearly visit with her healthcare provider for a blood pressure check and for other indicated health care.

5.13 Other Conditions

In women with hereditary angioedema, exogenous estrogens may induce or exacerbate symptoms of angioedema. Chloasma may occasionally occur, especially in women with a history of chloasma gravidarum. Women with a tendency to chloasma should avoid exposure to the sun or ultraviolet radiation while taking COCs.

6 ADVERSE REACTIONS

The following serious adverse reactions with the use of COCs are discussed elsewhere in the labeling:

- Serious cardiovascular events and smoking [see Boxed Warning and Warnings and Precautions (5.1)]
- Vascular events [see Warnings and Precautions (5.1)]
- Liver disease [see Warnings and Precautions (5.3)]

Adverse reactions commonly reported by COC users are:

- Irregular uterine bleeding
- Nausea
- Breast tenderness
- Headache

6.1 Clinical Trial Experience

Because clinical trials are conducted under widely varying conditions, adverse reaction rates observed in the clinical trials of a drug cannot be directly compared to the rates in the clinical trials of another drug and may not reflect the rates observed in practice.

The clinical trial that evaluated the safety and efficacy of Seasonique was a 12-month, randomized, multicenter, open-label study, which enrolled women aged 18-40, of whom 1,006 took at least one dose of Seasonique.

Adverse Reactions Leading to Study Discontinuation: 16.3% of the women discontinued from the clinical trial due to an adverse reaction; the most common adverse reactions (≥ 1% of women) leading to discontinuation were irregular and/or heavy uterine bleeding (5.9%), weight gain (2.4%), mood changes (1.5%), and acne (1.0%).

Common Treatment-Emergent Adverse Reactions (≥ 5% of women): irregular and/or heavy uterine bleeding (17%), weight gain (5%), acne (5%).

Serious Adverse Reactions: migraine, cholecystitis, cholelithiasis, pancreatitis, abdominal pain, and major depressive disorder.

6.2 Postmarketing Experience

The following adverse reactions have been identified during post-approval use of Seasonique. Because these reactions are reported voluntarily from a population of uncertain size, it is not possible to reliably estimate their frequency of establish a causal relationship to drug exposure.

Gastrointestinal disorders: abdominal distension, vomiting

General disorders and administration site conditions: chest pain, fatigue, malaise, edema peripheral, pain

Immune system disorders: hypersensitivity reaction

Investigations: blood pressure increased

Musculoskeletal and connective tissue disorders: muscle spasms, pain in extremity

Nervous system disorders: dizziness, loss of consciousness

Psychiatric disorders: insomnia

Reproductive and breast disorders: dysmenorrhea

Respiratory, thoracic and mediastinal disorders: pulmonary embolism, pulmonary thrombosis

Skin and subcutaneous tissue disorders: alopecia

Vascular disorders: thrombosis

7 DRUG INTERACTIONS

No drug-drug interaction studies were conducted with Seasonique.

7.1 Changes in Contraceptive Effectiveness Associated with Co-Administration of Other Products

If a woman on hormonal contraceptives takes a drug or herbal product that induces enzymes, including CYP3A4, that metabolize contraceptive hormones, counsel her to use additional contraception or a different method of contraception. Drugs or herbal products that induce such enzymes may decrease the plasma concentrations of contraceptive hormones, and may decrease the effectiveness of hormonal contraceptives or increase breakthrough bleeding. Some drugs or herbal products that may decrease the effectiveness of hormonal contraceptives include:

- barbiturates
- bosentan
- carbamazepine
- felbamate
- griseofulvin
- oxcarbazepine
- phenytoin
- rifampin
- St. John’s wort
- topiramate

HIV protease inhibitors and non-nucleoside reverse transcriptase inhibitors: Significant changes (increase or decrease) in the plasma levels of the estrogen and progestin have been noted in some cases of co-administration of HIV protease inhibitors or with non-nucleoside reverse transcriptase inhibitors.

Antibiotics: There have been reports of pregnancy while taking hormonal contraceptives and antibiotics, but clinical pharmacokinetic studies have not shown consistent effects of antibiotics on plasma concentrations of synthetic steroids.

Consult the labeling of all concurrently-used drugs to obtain further information about interactions with hormonal contraceptives or the potential for enzyme alterations.

7.2 Increase in Plasma Levels of Estradiol Associated with Co-Administered Drugs

Co-administration of atorvastatin and certain COCs containing ethinyl estradiol increase AUC values for ethinyl estradiol by approximately 20%. Ascorbic acid and acetaminophen may increase plasma ethinyl estradiol levels, possibly by inhibition of conjugation. CYP3A4 inhibitors such as itraconazole or ketoconazole may increase plasma hormone levels.

7.3 Changes in Plasma Levels of Co-Administered Drugs

COCs containing some synthetic estrogens (e.g., ethinyl estradiol) may inhibit the metabolism of other compounds. COCs have been shown to significantly decrease plasma concentrations of lamotrigine likely due to induction of lamotrigine glucuronidation. This may reduce seizure control; therefore, dosage adjustments of lamotrigine may be necessary. Consult the labeling of the concurrently-used drug to obtain further information about interactions with COCs or the potential for enzyme alterations.

8 USE IN SPECIFIC POPULATIONS

8.1 Pregnancy

There is little or no increased risk of birth defects in women who inadvertently use COCs during early pregnancy. Epidemiologic studies and meta-analyses have not found an increased risk of genital or non-genital birth defects (including cardiac anomalies and limb-reduction defects) following exposure to low dose COCs prior to conception or during early pregnancy.

The administration of COCs to induce withdrawal bleeding should not be used as a test for pregnancy. COCs should not be used during pregnancy to treat threatened or habitual abortion.

Women who do not breastfeed may start COCs no earlier than four to six weeks postpartum.

8.3 Nursing Mothers

When possible, advise the nursing mother to use other forms of contraception until she has weaned her child. Estrogen-containing COCs can reduce milk production in breastfeeding mothers. This is less likely to occur once breastfeeding is well established; however, it can occur at any time in some women. Small amounts of oral contraceptive steroids and/or metabolites are present in breast milk.

8.4 Pediatric Use

Safety and efficacy of Seasonique have been established in women of reproductive age. Safety and efficacy are expected to be the same for postpubertal adolescents under the age of 18 as for users 18 years and older. Use of Seasonique before menarche is not indicated.

8.5 Geriatric Use

Seasonique has not been studied in women who have reached menopause and is not indicated in this population.

8.6 Hepatic Impairment

No studies have been conducted to evaluate the effect of hepatic disease on the disposition of Seasonique. However, steroid hormones may be poorly metabolized in patients with impaired liver function. Acute or chronic disturbances of liver function may necessitate the discontinuation of COC use until markers of liver function return to normal. [See Contraindications (4) and Warnings and Precautions (5.3)].

8.7 Renal Impairment

No studies have been conducted to evaluate the effect of renal disease on the disposition of Seasonique.

10 OVERDOSAGE

There have been no reports of serious ill effects from overdose of oral contraceptives, including ingestion by children. Overdosage may cause withdrawal bleeding in females and nausea.

11 DESCRIPTION

Seasonique (levonorgestrel/ethinyl estradiol tablets and ethinyl estradiol tablets) is an extended-cycle oral contraceptive consisting of 84 light blue-green tablets each containing 0.15 mg of levonorgestrel, a synthetic progestogen and 0.03 mg of ethinyl estradiol, and 7 yellow tablets containing 0.01 mg of ethinyl estradiol.

The structural formulas for the active components are:

Levonorgestrel C21H28O2 MW: 312.4

Levonorgestrel is chemically 18,19-Dinorpregn-4-en-20-yn-3-one, 13-ethyl-17-hydroxy-, (17α)-, (-)-.

Ethinyl Estradiol C20H24O2 MW: 296.4

Ethinyl Estradiol is 19-Norpregna-1,3,5(10)-trien-20-yne-3,17-diol, (17α)-.

Each light blue-green tablet contains the following inactive ingredients: anhydrous lactose, D&C yellow no. 10 aluminum lake, FD&C blue no. 1 aluminum lake, FD&C yellow no. 6/Sunset yellow aluminum lake, hypromellose, lactose monohydrate, magnesium stearate, microcrystalline cellulose, titanium dioxide and triacetin.

Each yellow tablet contains the following inactive ingredients: anhydrous lactose, D&C yellow no. 10 aluminum lake, FD&C yellow no. 6/Sunset yellow aluminum lake, hypromellose, magnesium stearate, microcrystalline cellulose, polacrilin potassium, polyethylene glycol, polysorbate 80 and titanium dioxide.

12 CLINICAL PHARMACOLOGY

12.1 Mechanism of action

COCs lower the risk of becoming pregnant primarily by suppressing ovulation. Other possible mechanisms may include cervical mucus changes that inhibit sperm penetration and endometrial changes that reduce the likelihood of implantation.

12.3 Pharmacokinetics

Absorption

Ethinyl estradiol and levonorgestrel are absorbed with maximum plasma concentrations occurring within 2 hours after Seasonique administration. Levonorgestrel is completely absorbed after oral administration (bioavailability nearly 100%) and is not subject to first-pass metabolism. Ethinyl estradiol is absorbed from the gastrointestinal tract but, due to first-pass metabolism in gut mucosa and liver, the bioavailability of ethinyl estradiol is approximately 43%.

The daily exposure to levonorgestrel and ethinyl estradiol on Day 21, corresponding to the end of a typical 3-week contraceptive regimen, and on Day 84, at the end of an extended cycle regimen, were similar. There was no additional accumulation of ethinyl estradiol after dosing a 0.03 mg ethinyl estradiol tablet during Days 84-91. The mean plasma pharmacokinetic parameters of Seasonique following a single dose of one levonorgestrel/ethinyl estradiol combination tablet, for 84 days, in normal healthy women are reported in Table 3.

Table 3: Mean Pharmacokinetic Parameters for Seasonique during Daily One Tablet Dosing for 84 Days
 | AUC0-24 hr (mean ± SD) | Cmax (mean ± SD) | Tmax (mean ± SD)
 | Levonorgestrel
Day 1 | 18.2 ± 6.1 ng•hr/mL | 3.0 ± 1.0 ng/mL | 1.3 ± 0.4 hours
Day 21 | 64.4 ± 25.1 ng•hr/mL | 6.2 ± 1.6 ng/mL | 1.3 ± 0.4 hours
Day 84 | 60.2 ± 24.6 ng•hr/mL | 5.5 ± 1.6 ng/mL | 1.3 ± 0.3 hours
 | Ethinyl Estradiol
Day 1 | 509.3 ± 172.0 pg•hr/mL | 69.8 ± 26 pg/mL | 1.5 ± 0.3 hours
Day 21 | 837.1 ± 271.2 pg•hr/mL | 99.6 ± 31 pg/mL | 1.5 ± 0.3 hours
Day 84 | 791.5 ± 215.0 pg•hr/mL | 91.3 ± 32 pg/mL | 1.6 ± 0.3 hours

The effect of food on the rate and the extent of levonorgestrel and ethinyl estradiol absorption following oral administration of Seasonique has not been evaluated.

Distribution

The apparent volume of distribution of levonorgestrel and ethinyl estradiol are reported to be approximately 1.8 L/kg and 4.3 L/kg, respectively. Levonorgestrel is about 97.5 - 99% protein-bound, principally to sex hormone binding globulin (SHBG) and, to a lesser extent, serum albumin. Ethinyl estradiol is about 95 - 97% bound to serum albumin. Ethinyl estradiol does not bind to SHBG, but induces SHBG synthesis, which leads to decreased levonorgestrel clearance. Following repeated daily dosing of levonorgestrel/ethinyl estradiol oral contraceptives, levonorgestrel plasma concentrations accumulate more than predicted based on single-dose pharmacokinetics, due in part, to increased SHBG levels that are induced by ethinyl estradiol, and a possible reduction in hepatic metabolic capacity.

Metabolism

Following absorption, levonorgestrel is conjugated at the 17β-OH position to form sulfate and to a lesser extent, glucuronide conjugates in plasma. Significant amounts of conjugated and unconjugated 3α,5β-tetrahydrolevonorgestrel are also present in plasma, along with much smaller amounts of 3α,5α-tetrahydrolevonorgestrel and 16β-hydroxylevonorgestrel. Levonorgestrel and its phase I metabolites are excreted primarily as glucuronide conjugates. Metabolic clearance rates may differ among individuals by several-fold, and this may account in part for the wide variation observed in levonorgestrel concentrations among users.

First-pass metabolism of ethinyl estradiol involves formation of ethinyl estradiol-3-sulfate in the gut wall, followed by 2-hydroxylation of a portion of the remaining untransformed ethinyl estradiol by hepatic cytochrome P-450 3A4 (CYP3A4). Levels of CYP3A4 vary widely among individuals and can explain the variation in rates of ethinyl estradiol hydroxylation. Hydroxylation at the 4-, 6-, and 16- positions may also occur, although to a much lesser extent than 2-hydroxylation. The various hydroxylated metabolites are subject to further methylation and/or conjugation.

Excretion

About 45% of levonorgestrel and its metabolites are excreted in the urine and about 32% are excreted in feces, mostly as glucuronide conjugates. The terminal elimination half-life for levonorgestrel after a single dose of Seasonique was about 34 hours.

Ethinyl estradiol is excreted in the urine and feces as glucuronide and sulfate conjugates, and it undergoes enterohepatic recirculation. The terminal elimination half-life of ethinyl estradiol after a single dose of Seasonique was found to be about 18 hours.

Race

The effect of race on the pharmacokinetics of Seasonique has not been evaluated.

13 NONCLINICAL TOXICOLOGY

13.1 Carcinogenesis, Mutagenesis, Impairment of Fertility

[See Warnings and Precautions (5.2, 5.3)].

14 CLINICAL STUDIES

In a 12-month, multicenter, randomized, open-label clinical trial, 1,006 women aged 18-40 were studied to assess the safety and efficacy of Seasonique, completing the equivalent of 8,681 28-day cycles of exposure. The racial demographic of those enrolled was: Caucasian (80%), African-American (11%), Hispanic (5%), Asian (2%), and Other (2%). There were no exclusions for body mass index (BMI) or weight. The weight range of those women treated was 91 to 360 lbs., with a mean weight of 156 lbs. Among the women in the trial, 63% were current or recent hormonal contraceptive users, 26% were prior users (who had used hormonal contraceptives in the past but not in the 6 months prior to enrollment), and 11% were new starts. Of treated women, 14.8% were lost to follow-up, 16.3% discontinued due to an adverse event, and 12.9% discontinued by withdrawing their consent.

The pregnancy rate (Pearl Index [PI]) in women aged 18-35 years was 1.34 pregnancies per 100 women-years of use (95% confidence interval 0.54-2.75), based on 7 pregnancies that occurred after the onset of treatment and within 14 days after the last combination pill. Cycles in which conception did not occur, but which included the use of backup contraception, were not included in the calculation of the PI. The PI includes patients who did not take the drug correctly.

16 HOW SUPPLIED/STORAGE AND HANDLING

16.1 How Supplied

Seasonique tablets (levonorgestrel/ethinyl estradiol tablets and ethinyl estradiol tablets) are available in Extended-Cycle Tablet Dispensers (NDC 54868-6276-0), each containing a 13-week supply of tablets: 84 light blue-green tablets, each containing 0.15 mg of levonorgestrel and 0.03 mg ethinyl estradiol, and 7 yellow tablets each containing 0.01 mg of ethinyl estradiol. The light blue-green tablets are round, film-coated, biconvex, unscored tablets debossed with stylized b on one side and 555 on the other side. The yellow tablets are round, biconvex, film-coated, unscored tablets debossed with stylized b on one side and 556 on the other side.

Box of 1 Extended-Cycle Tablet Dispensers NDC 54868-6276-0

16.2 Storage Conditions

Store at 20° to 25° C (68° to 77° F) [See USP Controlled Room Temperature].

17 PATIENT COUNSELING INFORMATION

See FDA- Approved Patient Labeling

- Counsel patients that cigarette smoking increases the risk of serious cardiovascular events from COC use, and that women who are over 35 years old and smoke should not use COCs.
- Counsel patients that this product does not protect against HIV-infection (AIDS) and other sexually transmitted diseases.
- Counsel patients on Warnings and Precautions associated with COCs.
- Counsel patients to take one tablet daily by mouth at the same time every day. Instruct patients what to do in the event pills are missed. See WHAT TO DO IF YOU MISS PILLS section of FDA-Approved Patient Labeling.
- Counsel patients to use a back-up or alternative method of contraception when enzyme inducers are used with COCs.
- Counsel patients who are breastfeeding or who desire to breastfeed that COCs may reduce breast milk production. This is less likely to occur if breastfeeding is well established.
- Counsel any patient who starts COCs postpartum, and who has not yet had a period, to use an additional method of contraception until she has taken a light blue-green tablet for 7 consecutive days.
- Counsel patients that amenorrhea may occur. Pregnancy should be considered in the event of amenorrhea, and should be ruled out if amenorrhea is associated with symptoms of pregnancy, such as morning sickness or unusual breast tenderness.

DURAMED PHARMACEUTICALS, INC.
Subsidiary of Barr Pharmaceuticals, Inc. Pomona, New York 10970
11001500

Relabeling and Repackaging by:
Physicians Total Care, Inc.
Tulsa, OK 74146

FDA-Approved Patient Labeling

Guide for Using Seasonique

WARNING TO WOMEN WHO SMOKE

Do not use Seasonique if you smoke cigarettes and are over 35 years old. Smoking increases your risk of serious cardiovascular side effects from birth control pills, including death from heart attack, blood clots or stroke. This risk increases with age and the number of cigarettes you smoke.

Birth control pills help to lower the chances of becoming pregnant. They do not protect against HIV infection (AIDS) and other sexually transmitted diseases.

What Is Seasonique?

Seasonique is a birth control pill. It contains two female hormones, an estrogen called ethinyl estradiol, and a progestin called levonorgestrel.

How Well Does Seasonique Work?

Your chance of getting pregnant depends on how well you follow the directions for taking your birth control pills. The more carefully you follow the directions, the less chance you have of getting pregnant.

Based on the results of a single clinical study lasting 12 months, 1 to 3 women, out of 100 women, may get pregnant during the first year they use Seasonique.

The following chart shows the chance of getting pregnant for women who use different methods of birth control. Each box on the chart contains a list of birth control methods that are similar in effectiveness. The most effective methods are at the top of the chart. The box on the bottom of the chart shows the chance of getting pregnant for women who do not use birth control and are trying to get pregnant.

Fewer than 1 pregnancy per 100 women in one year | Fewer pregnancies | - Implants - Injections - Intrauterine devices - Sterilization
 |  | - Birth control pills - Skin patch - Vaginal rings with hormones
10-20 Pregnancies per 100 women in one year |  | - Condom - Diaphragm
10-20 Pregnancies per 100 women in one year |  | - No sex during the most fertile days of the monthly cycle - Spermicide - Withdrawal
85 or more pregnancies per 100 women in one year | More pregnancies | - No birth control

How Do I Take Seasonique?

1. Take one pill every day at the same time. If you miss pills you could get pregnant. This includes starting the pack late. The more pills you miss, the more likely you are to get pregnant.

2. Many women have spotting or light bleeding, or may feel sick to their stomach during the first few months of taking Seasonique. If you feel sick to your stomach, do not stop taking the pill. The problem will usually go away. If it doesn't go away, check with your healthcare provider.

3. Missing pills can also cause spotting or light bleeding, even when you take the missed pills later. On the days you take 2 pills to make up for missed pills, you could also feel a little sick to your stomach.

4. If you have trouble remembering to take Seasonique, talk to your healthcare provider about how to make pill-taking easier or about using another method of birth control.

Before you start taking Seasonique

1. Decide what time of day you want to take your pill. It is important to take it at about the same time every day.

2. Look at your Extended-Cycle Tablet Dispenser. Your Tablet Dispenser consists of 3 trays with cards that hold 91 individually sealed pills (a 13-week or 91-day cycle). The 91 pills consist of 84 light blue-green and 7 yellow pills. Trays 1 and 2 each contain 28 light blue-green pills (4 rows of 7 pills). Tray 3 contains 35 pills consisting of 28 light blue-green pills (4 rows of 7 pills) and 7 yellow pills (1 row of 7 pills).

3. Also find:

- Where on the first tray in the pack to start taking pills (upper left corner at the start arrow) and
- In what order to take the pills (follow the weeks and arrow).

4. Be sure you have ready at all times another kind of birth control (such as condoms or spermicides), to use as a back-up in case you miss pills.

When to Start Seasonique

1. Take the first light blue-green pill on the Sunday after your period starts, even if you are still bleeding. If your period begins on Sunday, start the first light blue-green pill that same day.

2. Use another method of birth control (such as condoms or spermicides) as a back-up method if you have sex anytime from the Sunday you start your first light blue-green pill until the next Sunday (first 7 days). If you have been using a different hormonal method of birth control (such as a different pill, the “patch,” or the “vaginal ring”), you need to use another method of birth control (such as condoms or spermicides) each time you have sex after stopping your old method of birth control until you have taken Seasonique for 7 days.

How to Take Seasonique

1. Take one pill at the same time every day until you have taken the last pill in the tablet dispenser.

- Do not skip pills even if you are experiencing spotting or bleeding or feel sick to your stomach (nausea).
- Do not skip pills even if you do not have sex very often.

2. When you finish a tablet dispenser

- After taking the last yellow pill, start taking the first light blue-green pill from a new Extended-Cycle Tablet Dispenser the very next day (this should be on a Sunday) regardless of when your period started.

3. If you miss your scheduled period when you are taking the yellow pills, contact your healthcare provider because you may be pregnant. If you are pregnant, you should stop taking Seasonique.

What To Do If You Miss Pills

If you MISS 1 light blue-green pill:

1. Take it as soon as you remember. Take the next pill at your regular time. This means you may take 2 pills in 1 day.

2. You do not need to use a back-up birth control method if you have sex.

If you MISS 2 light blue-green pills in a row:

1. Take 2 pills on the day you remember, and 2 pills the next day.

2. Then take 1 pill a day until you finish the pack.

3. You could become pregnant if you have sex in the 7 days after you miss two pills. You MUST use another birth control method (such as condoms or spermicide) as a back up for the 7 days after you restart your pills.

If you MISS 3 OR MORE light blue-green pills in a row:

1. Do not take the missed pills. Keep taking 1 pill every day as indicated on the pack until you have completed all of the remaining pills in the pack. For example: If you resume taking the pill on Thursday, take the pill under “Thursday” and do not take the missed pills. You may experience bleeding during the week following the missed pills.

2. You could become pregnant if you have sex during the days of missed pills or during the first 7 days after restarting your pills.

3. You MUST use a non-hormonal birth control method (such as condoms or spermicide) as a back-up when you miss pills and for the first 7 days after you restart your pills. If you do not have your period when you are taking the yellow pills, call your healthcare provider because you may be pregnant.

If you MISS ANY of the 7 yellow pills:

1. Throw away the missed pills.

2. Keep taking the scheduled pills until the pack is finished.

3. You do not need a back-up method of birth control.

Finally, if you are still not sure what to do about the pills you have missed

1. Use a back-up method anytime you have sex.

2. Keep taking one pill each day until you contact your healthcare provider.

Who Should Not Take Seasonique?

Your healthcare provider will not give you Seasonique if you have:

- Ever had breast cancer or any cancer that is sensitive to female hormones
- Liver disease, including liver tumors
- Ever had blood clots in your arms, legs, or lungs
- Ever had a stroke
- Ever had a heart attack
- Certain heart valve problems or heart rhythm abnormalities that can cause blood clots to form in the heart
- An inherited problem with your blood that makes it clot more than normal
- High blood pressure that medicine can't control
- Diabetes with kidney, eye, or blood vessel damage
- Certain kinds of severe migraine headaches with aura, numbness, weakness or changes in vision

Also, do not take birth control pills if you:

- Smoke and are over 35 years old
- Are pregnant

Birth control pills may not be a good choice for you if you have ever had jaundice (yellowing of the skin or eyes) caused by pregnancy.

What Else Should I Know About Taking Seasonique?

Birth control pills do not protect you against any sexually transmitted disease, including HIV, the virus that causes AIDS.

Do not skip any pills, even if you do not have sex often.

Birth control pills should not be taken during pregnancy. However, birth control pills taken by accident during pregnancy are not known to cause birth defects.

If you are breastfeeding, consider another birth control method until you are ready to stop breastfeeding. Birth control pills that contain estrogen, like Seasonique, may decrease the amount of milk you make. A small amount of the pill's hormones pass into breast milk.

Tell your healthcare provider about all medicines and herbal products that you take. Some medicines and herbal products may make birth control pills less effective, including:

- barbiturates
- bosentan
- carbamazepine
- felbamate
- griseofulvin
- oxcarbazepine
- phenytoin
- rifampin
- St. John’s wort
- topiramate

Consider using another birth control method when you take medicines that may make birth control pills less effective.

Birth control pills may interact with lamotrigine, an anticonvulsant used for epilepsy. This may increase the risk of seizures, so your physician may need to adjust the dose of lamotrigine.

If you have vomiting or diarrhea, your birth control pills may not work as well. Use another birth control method, like condoms or a spermicide, until you check with your healthcare provider.

What Are The Most Serious Risks Of Taking Birth Control Pills?

Like pregnancy, birth control pills increase the risk of serious blood clots, especially in women who have other risk factors, such as smoking, obesity, or age > 35. It is possible to die from a problem caused by a blood clot, such as a heart attack or a stroke. Some examples of serious blood clots are blood clots in the:

- Legs (thrombophlebitis)
- Lungs (pulmonary embolus)
- Eyes (loss of eyesight)
- Heart (heart attack)
- Brain (stroke)

Women who take birth control pills may get:

- High blood pressure
- Gallbladder problems
- Rare cancerous or noncancerous liver tumors

All of these events are uncommon in healthy women.

Call your healthcare provider right away if you have:

- Persistent leg pain
- Sudden shortness of breath
- Sudden blindness, partial or complete
- Severe pain in your chest
- Sudden, severe headache unlike your usual headaches
- Weakness or numbness in an arm or leg, or trouble speaking
- Yellowing of the skin or eyeballs

What Are Common Side Effects Of Birth Control Pills?

The most common side effects of birth control pills are:

- Spotting or bleeding between menstrual periods
- Nausea
- Breast tenderness
- Headache

These side effects are usually mild and usually disappear with time.

Less common side effects are:

- Acne
- Less sexual desire
- Bloating or fluid retention
- Blotchy darkening of the skin, especially on the face
- High blood sugar, especially in women who already have diabetes
- High fat levels in the blood
- Depression, especially if you have had depression in the past. Call your healthcare provider immediately if you have any thoughts of harming yourself.
- Problems tolerating contact lenses
- Weight changes

This is not a complete list of possible side effects. Talk to your healthcare provider if you develop any side effects that concern you. You may report side effects to the FDA at 1-800-FDA-1088.

No serious problems have been reported from a birth control pill overdose, even when accidentally taken by children.

Do Birth Control Pills Cause Cancer?

Birth control pills do not appear to cause breast cancer. However, if you have breast cancer now, or have had it in the past, do not use birth control pills because some breast cancers are sensitive to hormones.

Women who use birth control pills may have a slightly higher chance of getting cervical cancer. However, this may be due to other reasons such as having more sexual partners.

What Should I Know About My Period When Taking Seasonique?

When you take Seasonique, which has a 91-day extended dosing cycle, you should expect to have 4 scheduled periods per year (bleeding when you are taking the 7 yellow pills). Each period is likely to last about 3 days. However, you will probably have more bleeding or spotting between your scheduled periods than if you were using a birth control pill with a 28-day dosing cycle. During the first Seasonique 91-day treatment cycle, about 3 in 10 women may have 20 or more days of unplanned bleeding or spotting. This bleeding or spotting tends to decrease with time. Do not stop taking Seasonique because of this bleeding or spotting. If the spotting continues for more than 7 consecutive days or if the bleeding is heavy, call your healthcare provider.

What If I Miss My Scheduled Period When Taking Seasonique?

You should consider the possibility that you are pregnant if you miss your scheduled period (no bleeding on the days that you are taking yellow tablets). Since scheduled periods are less frequent when you are taking Seasonique, notify your healthcare provider that you have missed your period and that you are taking Seasonique. Also notify your healthcare provider if you have symptoms of pregnancy such as morning sickness or unusual breast tenderness. It is important that your healthcare provider evaluates you to determine if you are pregnant. Stop taking Seasonique if it is determined that you are pregnant.

What If I Want To Become Pregnant?

You may stop taking the pill whenever you wish. Consider a visit with your healthcare provider for a pre-pregnancy checkup before you stop taking the pill.

General Advice About Seasonique

Your healthcare provider prescribed Seasonique for you. Do not share Seasonique with anyone else. Keep Seasonique out of the reach of children.

If you have concerns or questions, ask your healthcare provider. You may also ask your healthcare providers for a more detailed label written for medical professionals.

DURAMED PHARMACEUTICALS, INC.
Subsidiary of Barr Pharmaceuticals, Inc. Pomona, New York 10970
11001500
Revised July 2010

PRINCIPAL DISPLAY PANEL

seasonique®

levonorgestrel / ethinyl estradiol 0.15 mg / 0.03 mg TABLETS
and ethinyl estradiol 0.01 mg TABLETS

1 Extended-Cycle
Tablet Dispensers,
of 91 Tablets Each
NDC 54868-6276-0

Contains 1 Extended-Cycle Tablet Dipsensers, each containing 91 tablets: 84 light blue-green tablets, each containing 0.15 mg levonorgestrel and 0.03 mg ethinyl estradiol, and 7 yellow tablets each containing 0.01 mg ethinyl estradiol.

Store at 20° to 25° C (68° to 77° F) [See USP Controlled Room Temperature].